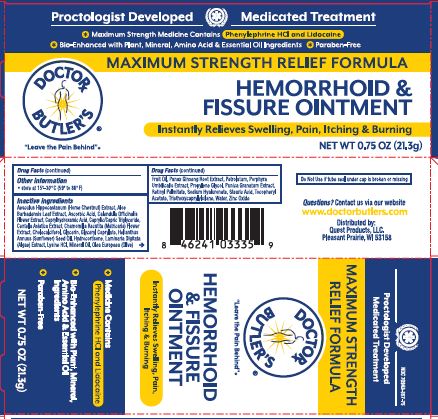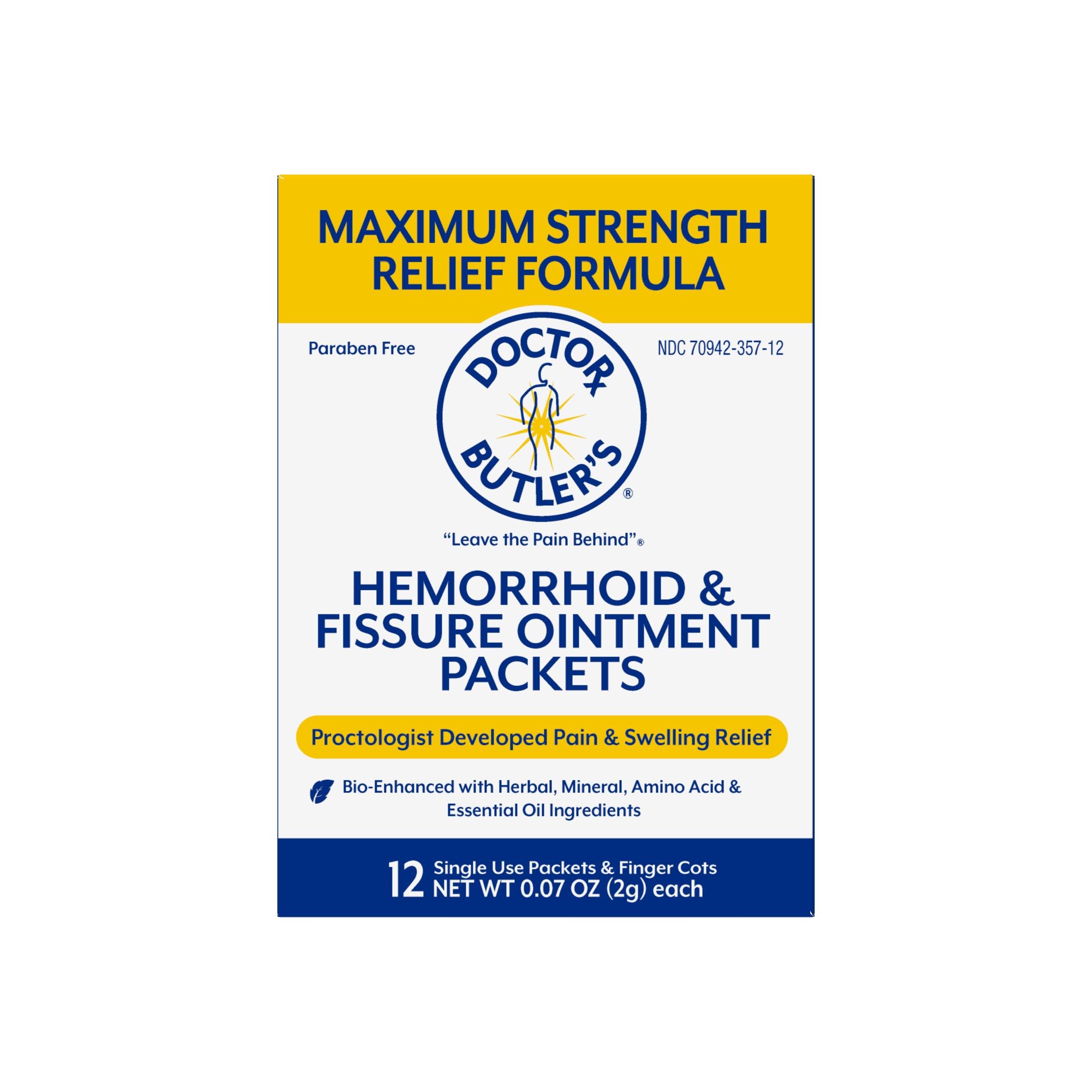 DRUG LABEL: Dr Butlers Hemorrhoid and Fissure PF
NDC: 70942-357 | Form: OINTMENT
Manufacturer: Beyond Health P.A.
Category: otc | Type: HUMAN OTC DRUG LABEL
Date: 20251126

ACTIVE INGREDIENTS: LIDOCAINE 4 g/100 g; PHENYLEPHRINE HYDROCHLORIDE 0.25 g/100 g
INACTIVE INGREDIENTS: HORSE CHESTNUT; ALOE; ASCORBIC ACID; CALENDULA OFFICINALIS FLOWER; CAPRYLHYDROXAMIC ACID; CENTELLA ASIATICA; CHOLECALCIFEROL; SUNFLOWER OIL; HYDROCORTISONE; LYSINE HYDROCHLORIDE; MINERAL OIL; CAPRYLIC/CAPRIC TRIGLYCERIDE; OLIVE OIL; ASIAN GINSENG; MATRICARIA CHAMOMILLA FLOWERING TOP OIL; PETROLATUM; PROPYLENE GLYCOL; PUNICA GRANATUM ROOT BARK; GLYCERYL CAPRYLATE; VITAMIN A PALMITATE; LAMINARIA DIGITATA; HYALURONATE SODIUM; PORPHYRA UMBILICALIS; STEARIC ACID; .ALPHA.-TOCOPHEROL ACETATE; TRIETHOXYCAPRYLYLSILANE; WATER; GLYCERIN; ZINC OXIDE

Dr Butler Hemorrhoid & Fissure Ointment PF

Active Ingredients

Lidocaine USP 4%

Phenylephrine HCl 0.25%

Purpose

Analgesic (pain relief)

Vasoconstrictor

Uses

- temporarily shrinks hemorrhoidal tissue
- for the temporary relief of pain, soreness, or burning
- helps relieve the local itching and discomfort associated with hemorrhoids

Warnings

For external use only including the skin of the anal canal.

When using this product

- do not exceed recommended dosage unless directed by a doctor
- when using finger cots or an applicator, apply externally or to the skin of the anal canal only. Do not put this product into the rectum

Ask a doctor before use if you have

- allergies to any of the components of this product
- difficulty in urination due to enlargement of the prostate gland
- Diabetes
- Heart Disease
- High Blood Pressure
- Thyroid Disease
- presently taking a prescription for high blood pressure or depression

Stop use and ask a doctor if

- condition worsens or does not improve within seven (7) days
- bleeding occurs
- an allergic reation develops
- the symptom being treated does not subside or if redness, irritation, swelling, pain or other symptoms develop or increase

If pregnant or breast-feeding

as a health care professional before use.

Keep out of reach of children

if swallowed, seek medical help or contact a Poison Control Center right away.

Directions

- children under 12 years of age consult your pediatrician.
- adults: apply to affected area up to 4 times daily.
- cleanse the affected area with mild soap and warm water, rinse thoroughly, and then gently dry (patting or blotting) with tissue or soft cloth before use.
- to use dispensing cap, attach it to tube, lubricate well, then apply externally to the skin of the anal canal only. Thoroughly cleanse dispensing cap after use with mild soap and warm water and rinse thoroughly

Other Information

- store at 15º-30º C (59º-86º F)

Inactive Ingedients

Aesculus hippocastanum (horse chestnut) extract, aloe barbadensis leaf extract, ascorbic acid, calendula officinalis flower extract, caprylhydroxamic acid, caprylic/capric triglyceride, centella asiatica extract, chamomile recutita (matricaria) flower extract, cholecalciferol, glycerin, glyceryl caprylate, helianthus annuus (sunflower) seed oil, hydrocortisone, laminaria digitata (algae) extract, lysine HCl, mineral oil, olea europaea (olive) fruit oil, panax ginseng root extract, petrolatum, porphyria umbilicalis extract, propylene glycol, punica granatum fruit extract, retinyl palmitate, sodium hyaluronate, stearic acid, tocopheryl acetate, triethoxycaprylysilane, water, zinc oxide